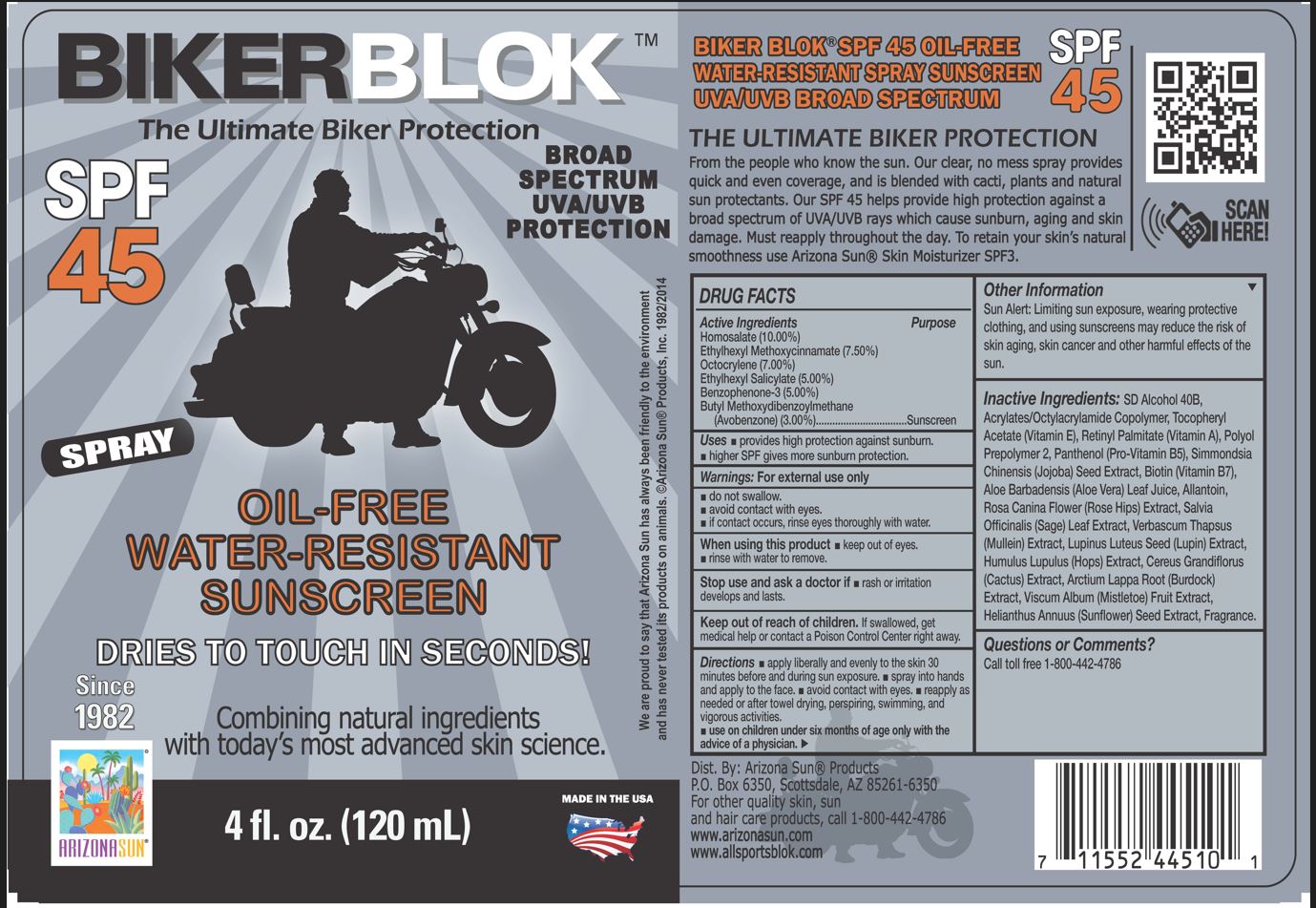 DRUG LABEL: Arizona Sun SPF 45 Bikerblok Sunscreen
NDC: 61973-109 | Form: SPRAY
Manufacturer: Arizona Sun Products
Category: otc | Type: HUMAN OTC DRUG LABEL
Date: 20240221

ACTIVE INGREDIENTS: OCTISALATE 50 mg/1 g; OXYBENZONE 50 mg/1 g; OCTOCRYLENE 70 mg/1 g; AVOBENZONE 30 mg/1 g; OCTINOXATE 75 mg/1 g; HOMOSALATE 100 mg/1 g
INACTIVE INGREDIENTS: SUNFLOWER SEED; VISCUM ALBUM FRUIT; ALCOHOL; ACRYLATE/ISOBUTYL METHACRYLATE/N-TERT-OCTYLACRYLAMIDE COPOLYMER (40000 MW); LUPINUS LUTEUS SEED; SELENICEREUS GRANDIFLORUS FLOWER; ALLANTOIN; VITAMIN A PALMITATE; PANTHENOL; ARCTIUM LAPPA ROOT; PPG-12/SMDI COPOLYMER; ROSA CANINA FLOWER; BIOTIN; ALOE VERA LEAF; SAGE; MULLEIN LEAF; .ALPHA.-TOCOPHEROL ACETATE; SIMMONDSIA CHINENSIS SEED; HOPS

Bikerblok SPF 45 Spray

Active Ingredients

Homosalate (10.00%), Ethylhexyl Methoxycinnamate (7.50%), Octocrylene (7.00%), Ethylhexyl Salicylate (5.00%), Benzophenone-3 (5.00%), Butyl Methoxydibenzoylmethane (Avobenzone) (3.00%)

Purpose

Sunscreen

Uses

Provides high sunburn protection. Higher SPF gives more sunburn protection

Warnings

For external use only. Do not swallow. Avoid contact with eyes. If contact occurs, rinse eyes thouroughly with water.

When using this product

keep out of eyes. Rinse with water to remove.

Stop use and ask a doctor if

rash or irritation develops and lasts.

Keep out of the reach of children.

If swallowed get medical help or contact a poison control center right away.

Directions

Apply liberally and evenly to the skin 30 minutes before and during sun exposure. Spray into hands and apply to the face. Avoid contact with eyes. Reapply as needed or after towel drying, perspiring, swimming, and vigorous activities. Use on children under six months of age only wih the advise of a physician.

Other Information

Sun Alert: Limiting sun exposure, wearing protective clothing, and using suscreen may reduce the risk of skin aging, skin cancer and other harmful effects of the sun.

Inactive Ingredients

SD Alcohol 40B, Acrylates/ Octylacrylamide Copolymer, Tocopheryl Acetate (Vitamin E), Retinyl Palmitate, Polyol Prepolymer 2, Panthenol, Simmondsia Chinensis (Jojoba) Seed Extract, Biotin, Aloe Barbadensis (Aloe Vera) Leaf Juice, Allantoin, Rosa Canina Flower (Rose Hips) Extract, Salvia Officinalis (Sage) Leaf Extract, Verbascum Thapsus (Mullein) Extract, Lupinus Luteus Seed (Lupin) Extract, Humulus Lupulus (Hops) Extract, Cereus Grandiflorus (Cactus) Extract, Arctium Lappa Root (Burdock) Extract, Viscum Album (Mistletoe) Fruit Extract, Helianthus Annuus (Sunflower) Seed Extract, Fragrance

Questions or Comments?

Call toll free 1-800-442-4786